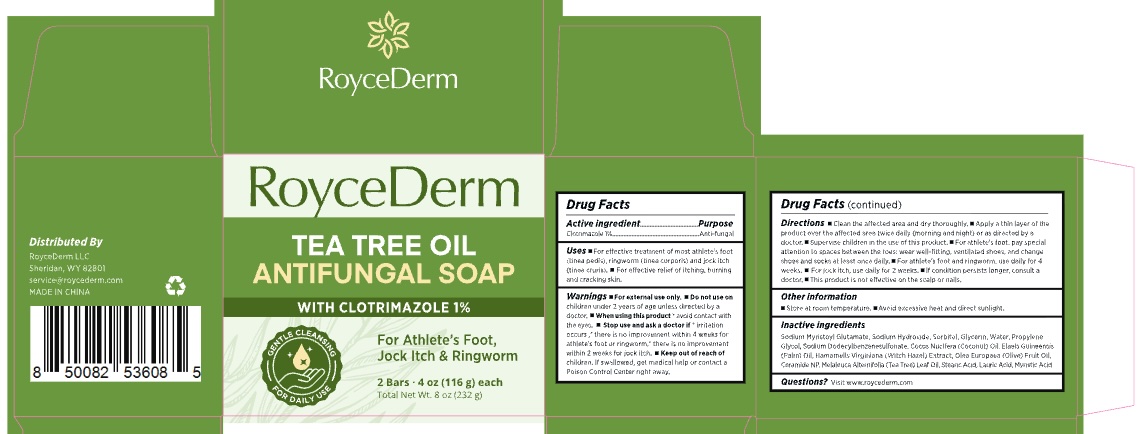 DRUG LABEL: RoyceDerm Tea Tree Oil Antifungal soap.
NDC: 85424-004 | Form: SOAP
Manufacturer: RoyceDerm LLC
Category: otc | Type: HUMAN OTC DRUG LABEL
Date: 20260213

ACTIVE INGREDIENTS: CLOTRIMAZOLE 2.32 g/232 g
INACTIVE INGREDIENTS: COCONUT OIL; STEARIC ACID; SODIUM GLUTAMATE; SODIUM DODECYLBENZENESULFONATE; GLYCERIN; SODIUM HYDROXIDE; AQUA; WITCH HAZEL; MYRISTIC ACID; PROPYLENE GLYCOL; SODIUM MYRISTOYL GLUTAMATE; SODIUM MYRISTATE; MELALEUCA ALTERNIFOLIA (TEA TREE) LEAF OIL; OLEA EUROPAEA (OLIVE) FRUIT OIL

NDC更新 - 85424-004

ACTIVE INGREDIENT

Clotrimazole 1%

PURPOSE

Anti-fungal

INDICATIONS AND USAGE

- For effective treatment of most athlete's foot(tinea pedis), ringworm (tinea corporis) and jock itch(tinea cruris).
- For effective relief of itching, burning and cracking skin.

DOSAGE AND ADMINISTRATION

- Clean the affected area and dry thoroughly.product over the affected area twice daily (morning and night) doctor.
- Supervise children in the use of this product.
- For attention to spaces between the toes; wear well-fitting, ventshoes and socks at least once daily.
- For athlete's foot and rweeks.
- For jock itch, use daily for 2 weeks.
- If condition pdoctor.
- This product is not effective on the scalp or nails.

OTHER SAFETY INFORMATION

- Store at room temperature
- Avoid excessive heat and direct sunlight.

WARNINGS

For external use only.

DO NOT USE

on children under 2 years of age unless directed by adoctor.

When using this product

avoid contact withthe eyes.

Stop use and ask a doctor if

irritationoccurs, there is no improvement within 4 weeks forathlete's foot or ringworm, there is no improvementwithin 2 weeks for jock itch.

KEEP OUT OF REACH OF CHILDREN

If swallowed, get medical help or contact aPoison Control Center right away.

INACTIVE INGREDIENT

Sodium Myristoyl Glutamate, Sodium Hydroxide, Sorbitol, Glycerin, Water, Propylene Glycol, Sodium Dodecylbenzenesulfonate, Cocos Nucifera (Coconut) OIl, Elaels Guineensis(Palm) Oil, Hamamelis Virginiana (Witch Hazel) Extract, Olea Europaea (Olive) Fruit Oil,Ceramide NP, Melaleuca Alternifolia (Tea Tree) Leaf Oil, Stearic Acid, Lauric Acid, Myristic Acid

QUESTIONS

visit www.roycederm.com